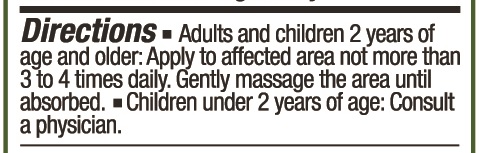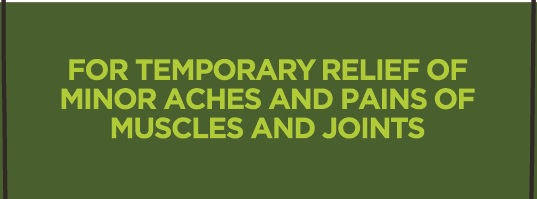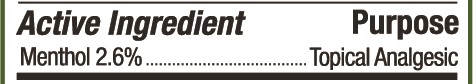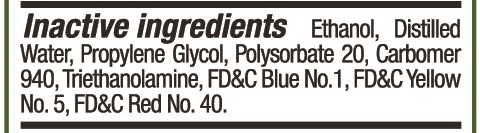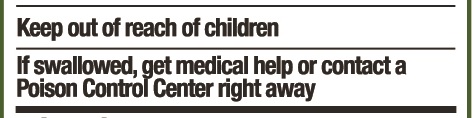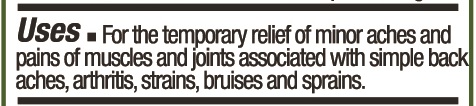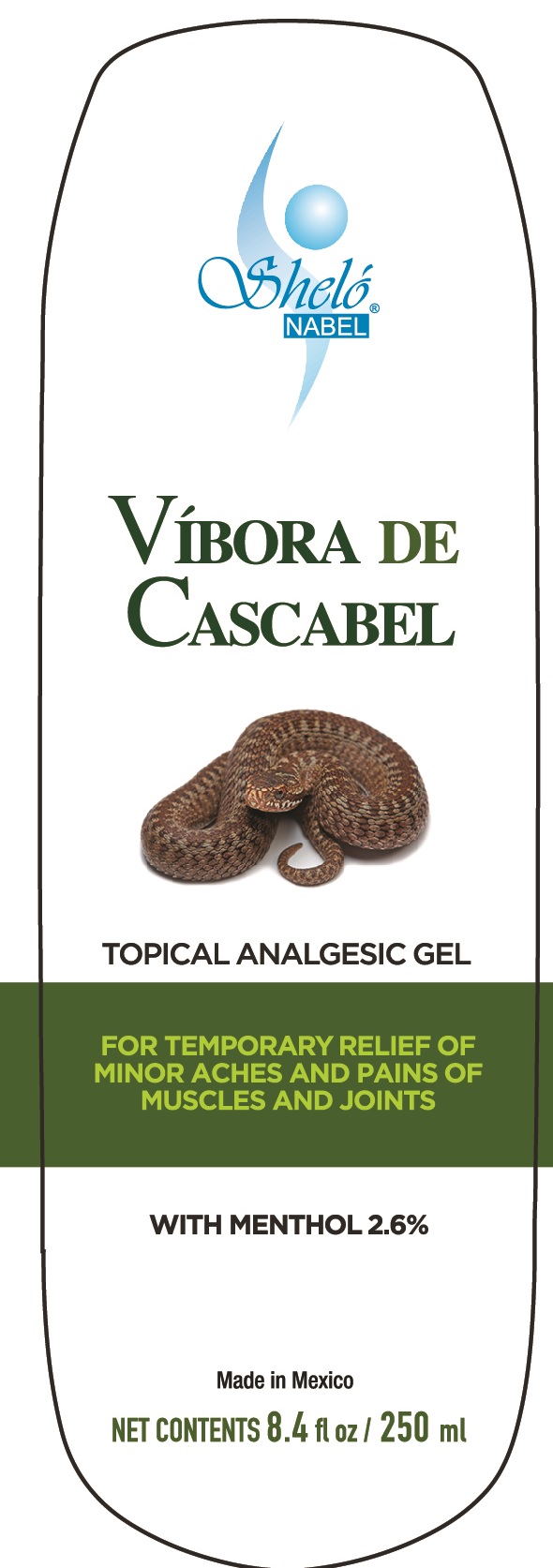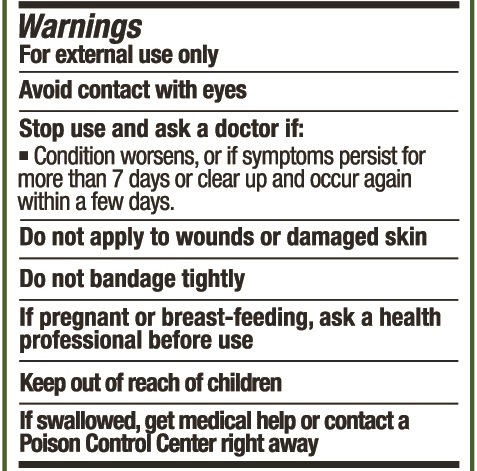 DRUG LABEL: Shelo NABEL Vibora de Cascabel Topical Analgesic Gel 250 ml
NDC: 71424-1070 | Form: GEL
Manufacturer: Corporativo Serysi S de R L de C V
Category: otc | Type: HUMAN OTC DRUG LABEL
Date: 20191015

ACTIVE INGREDIENTS: MENTHOL, UNSPECIFIED FORM 2.6 mg/100 g
INACTIVE INGREDIENTS: POLYSORBATE 20

Sheló NABEL Víbora de Cascabel Topical Analgesic Gel 250 Ml.